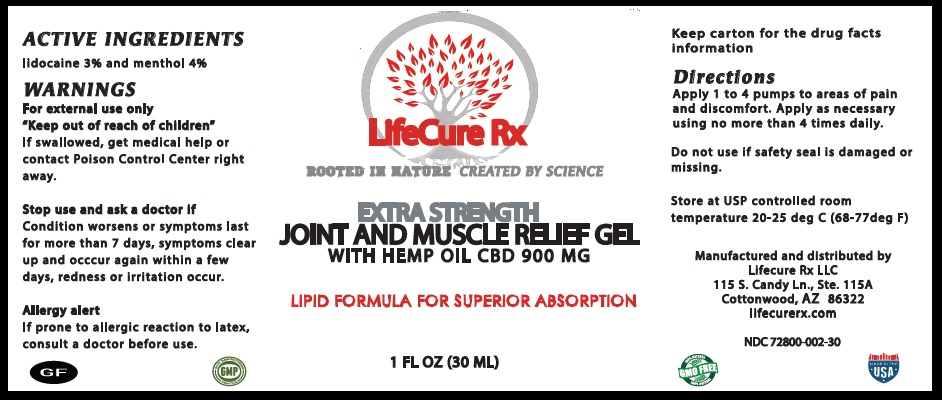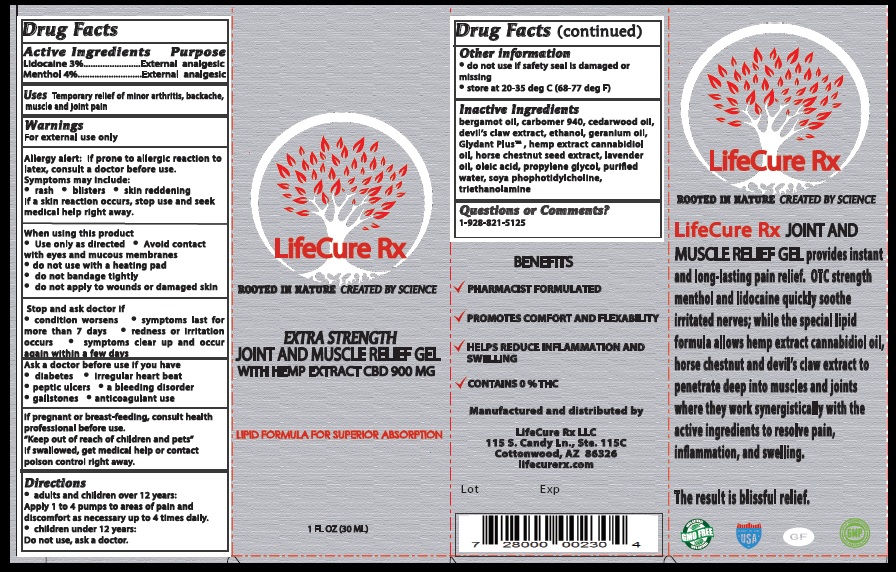 DRUG LABEL: EXTRA STRENGTH AND MUSCLE RELIEF 900 mg
NDC: 72800-002 | Form: GEL
Manufacturer: Lifecure Rx Specialty Pharmacy
Category: otc | Type: HUMAN OTC DRUG LABEL
Date: 20190318

ACTIVE INGREDIENTS: MENTHOL 40 mg/1 mL; LIDOCAINE 30 mg/1 mL
INACTIVE INGREDIENTS: BERGAMOT OIL; CARBOMER 934; JUNIPERUS VIRGINIANA OIL; HARPAGOPHYTUM PROCUMBENS ROOT; ALCOHOL; GERANIUM THUNBERGII FLOWERING TOP; HEMP; HORSE CHESTNUT; LAVANDULA ANGUSTIFOLIA SUBSP. ANGUSTIFOLIA FLOWER; OLEIC ACID; 1,2-DILINOLEOYL-SN-GLYCERO-3-PHOSPHOCHOLINE; PROPYLENE GLYCOL; WATER; TROLAMINE

EXTRA STRENGTH JOINT AND MUSCLE RELIEF GEL

Uses

Temporary relief of minor arthritis, backache, muscle and joint pain

Warnings

For external use only
Allergy alert: If prone to allergic reaction to latex, consult a doctor before use. Symptoms may include: • rash • blisters • skin reddening
If a skin reaction occurs, stop use and seek medical help right away.

Directions

• adults and children 12 and older: Apply 1 to 4 pumps to areas of pain and discomfort. Reapply as necessary using no more than 4 times daily.
• children under the age of 12: Do not use, ask a doctor

When using this product:

• Use only as directed • Avoid contact with eyes and mucous membranes • do not use with a heating pad • do not bandage tightly

• do not apply to wounds or damaged skin

Stop and ask doctor if

• condition worsens • symptoms last for more than 7 days • symptoms clear up and occur again within a few days • redness or irritation occurs

storage

• Store at 20-35 deg C (68-77deg F).

Keep out of reach of children and pets

If swallowed, get medical help or contact poison control right away.

Active Ingredients & Purpose

Menthol 4%----------------- Analgesic

Lidocaine 3%--------------- Analgesic

Inactive Ingredient

bergamot oil, carbomer 940, caderwood oil, devil' claw extract, ethanol, geranium oil, Glydant Plus, hemp extract cannabidiol oil, horse chestnut seed extract, lavender oil, oleic acid, propylene glycol, purified water, soya photidylcholine, triethanolamine.